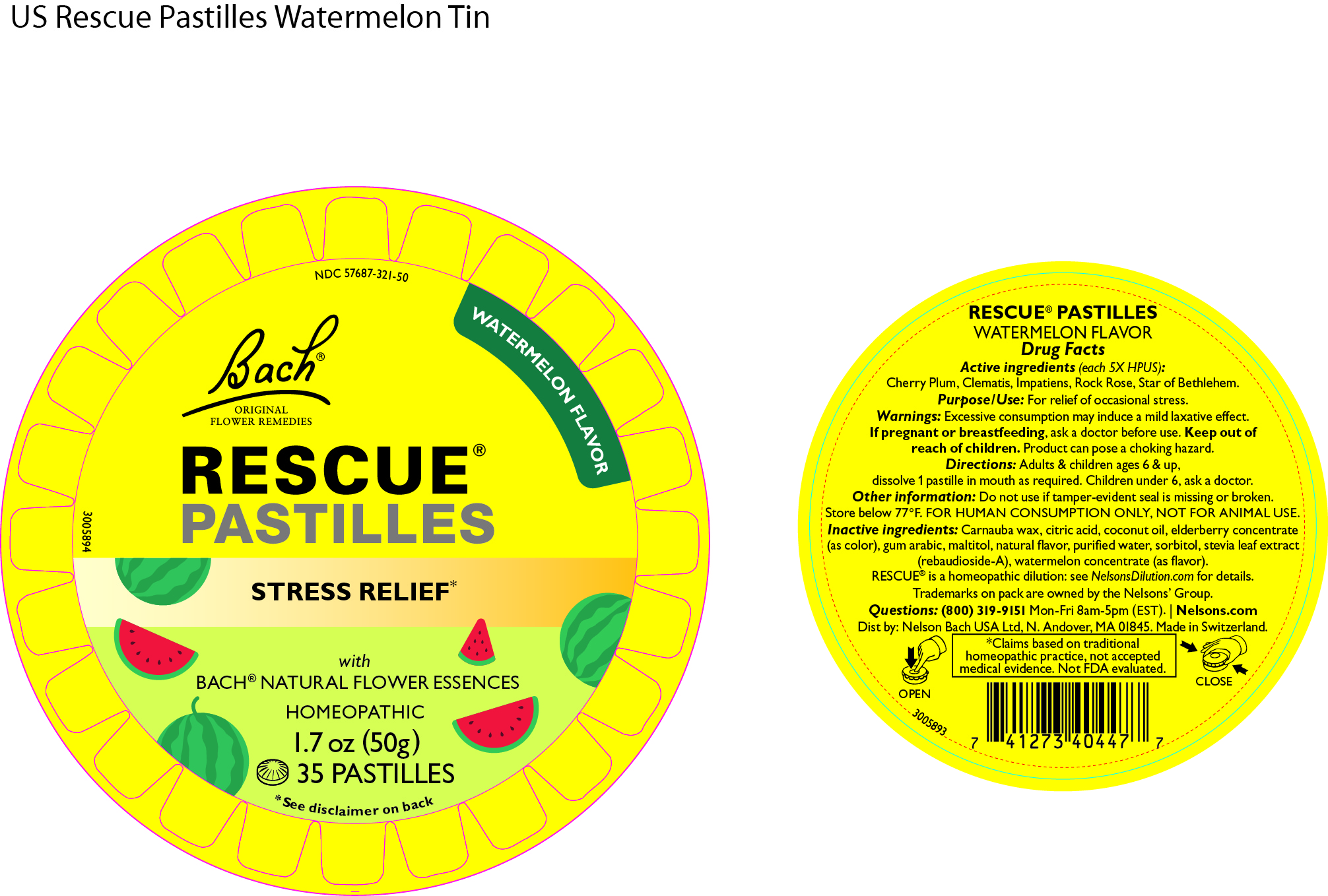 DRUG LABEL: Rescue Pastilles Watermelon Flavour
NDC: 57687-321 | Form: LOZENGE
Manufacturer: Nelson Bach USA Ltd
Category: homeopathic | Type: HUMAN OTC DRUG LABEL
Date: 20240827

ACTIVE INGREDIENTS: ORNITHOGALUM UMBELLATUM FLOWERING TOP 5 [hp_X]/1 1; PRUNUS CERASIFERA FLOWER 5 [hp_X]/1 1; CLEMATIS VITALBA FLOWER 5 [hp_X]/1 1; HELIANTHEMUM NUMMULARIUM FLOWER 5 [hp_X]/1 1; IMPATIENS GLANDULIFERA FLOWER 5 [hp_X]/1 1
INACTIVE INGREDIENTS: WATER; CARNAUBA WAX; STEVIOL; SORBITOL SOLUTION 70%; MALTITOL; EUROPEAN ELDERBERRY JUICE; WATERMELON; CITRIC ACID MONOHYDRATE; ACACIA

Rescue Watermelon Pastilles

Active ingredients (each 5X HPUS): Cherry Plum, Clematis, Impatiens, Rock Rose, Star of Bethlehem

Purpose / Use

For the relief of occasional stress

Warnings

Excessive consumption may induce a mild laxative effect. If pregnant or breastfeeding, ask a doctor before use. Keep out of reach of children. Product can pose a choking hazard.

Directions

Adults and children aged 6 and older, dissolve 1 pastilles in the mouth as required. Children under 6, ask a doctor.

Inactive Ingredients

carnauba wax, citric acid, coconut oil, elderberry concentrate, gum arabic, maltitol, natural flavour, purified water, sorbitol, stevia leaf extract (rebaudioside-A), watermelon concentrate (as flavour).

Other information

Do not use if tamper-evident seal is missing or broken. Store below 77o F. For human consumption only, not for animal use.

Questions

(800) 319-9151 Mon-Fri 8am-5pm (EST)

Distributed by

Nelson Bach USA Ltd, N Andover, MA 01845

OTC Purpose

For the relief of occasional stress

Keep out of reach of children. Product can pose a choking hazard.

PACKAGE LABEL

NDC 57687-321-50

Watermelon Flavour

Bach Original Flower Remedies

Rescue Pastilles

Stress Relief*

With Bach Natural Flower Essences

Homeopathic

1.7oz (50g)

35 Pastilles

*see disclaimer on back